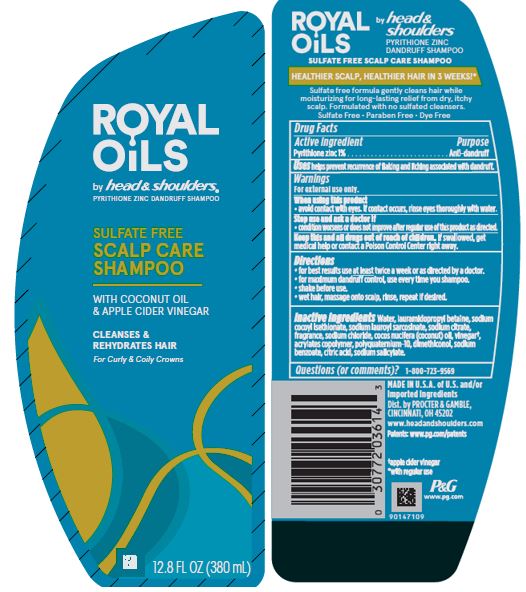 DRUG LABEL: Royal Oils by Head and Shoulders Sulfate Free Scalp Care
NDC: 69423-608 | Form: SHAMPOO
Manufacturer: The Procter & Gamble Manufacturing Company
Category: otc | Type: HUMAN OTC DRUG LABEL
Date: 20250108

ACTIVE INGREDIENTS: PYRITHIONE ZINC 1 g/100 mL
INACTIVE INGREDIENTS: COCONUT OIL; CITRIC ACID MONOHYDRATE; WATER; DIMETHICONOL GUM; LAURAMIDOPROPYL BETAINE; SODIUM CITRATE; SODIUM COCOYL ISETHIONATE; SODIUM LAUROYL SARCOSINATE; SODIUM SALICYLATE; SODIUM CHLORIDE; SODIUM BENZOATE; APPLE CIDER VINEGAR; POLYQUATERNIUM-10 (30000 MPA.S AT 2%); BUTYL ACRYLATE/METHYL METHACRYLATE/METHACRYLIC ACID COPOLYMER (18000 MW)

Royal Oils by Head and Shoulders Sulfate Free Scalp Care Shampoo

Drug Facts

Active ingredient

Pyrithione zinc 1%

Purpose

Anti-dandruff

Uses

helps prevent recurrence of flaking and itching associated with dandruff.

Warnings

For external use only.

When using this product

- avoid contact with eyes. If contact occurs, rinse eyes thoroughly with water.

Stop use and ask a doctor if

- condition worsens or does not improve after regular use of this product as directed.

KEEP OUT OF REACH OF CHILDREN

Keep this and all drugs out of reach of children. If swallowed, get medical help or contact a Poison Control Center right away.

Directions

- for best results use at least twice a week or as directed by a doctor.
- for maximum dandruff control, use every time you shampoo.
- shake before use.
- wet hair, massage onto scalp, rinse, repeat if desired.

Inactive ingredients

Water, lauramidopropyl betaine, sodium cocoyl isethionate, sodium lauroyl sarcosinate, sodium citrate, fragrance, sodium chloride, cocos nucifera (coconut) oil, vinegar†, acrylates copolymer, polyquaternium-10, dimethiconol, sodium benzoate, citric acid, sodium salicylate.

Questions (or comments)?

1-800-723-9569

Dist. by PROCTER & GAMBLE,
CINCINNATI, OH 45202

PRINCIPAL DISPLAY PANEL - 380 mL Bottle Label

ROYAL OILS

by head & shoulders ®

PYRITHIONE ZINC DANDRUFF SHAMPOO

SULFATE FREE

SCALP CARE

SHAMPOO

WITH COCONUT OIL

& APPLE CIDER VINEGAR

12.8 FL OZ (380 mL)